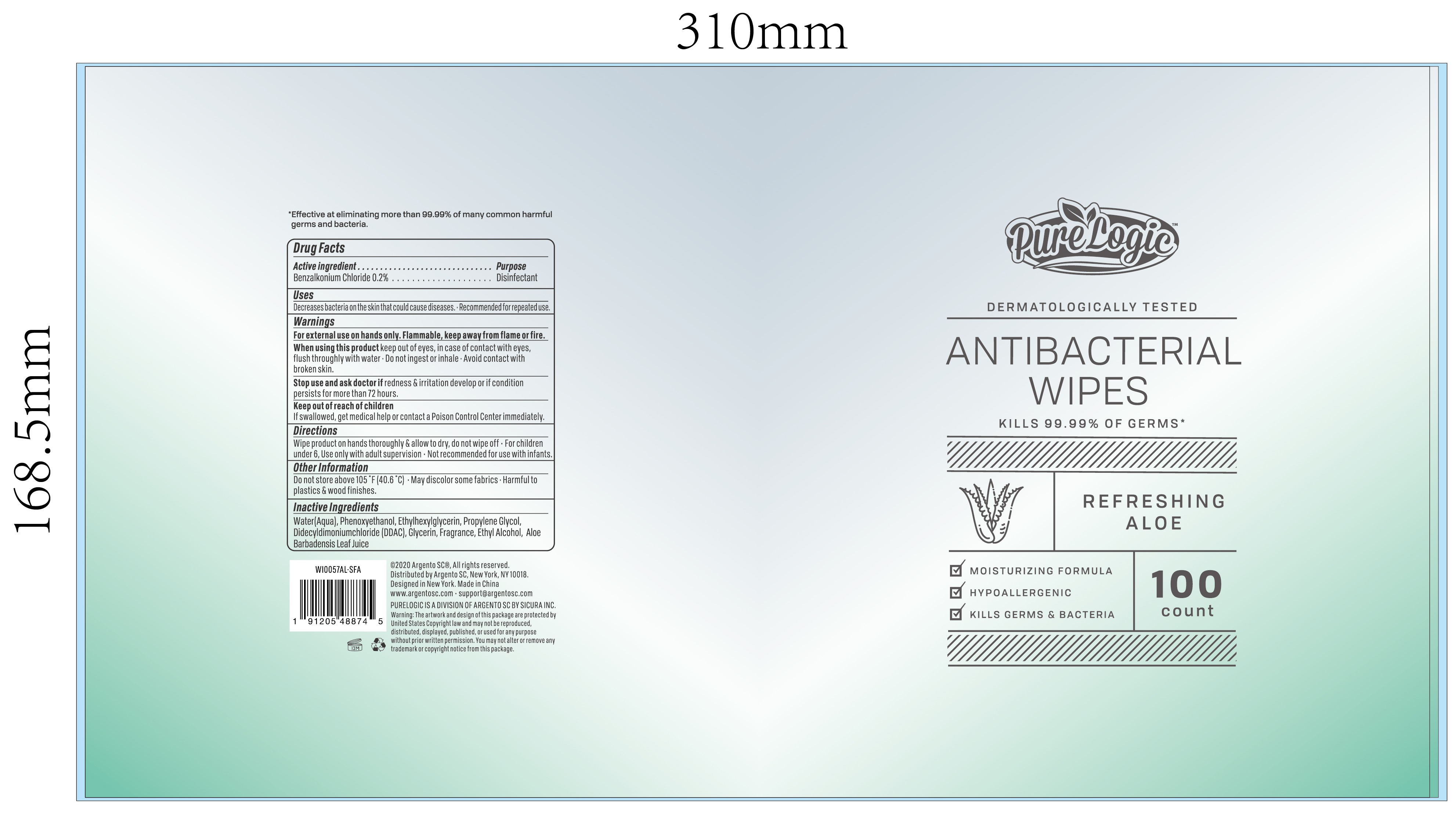 DRUG LABEL: PURELOGIC 100CT ALOE ANTIBACTERIAL WIPE CANISTER
NDC: 77731-104 | Form: CLOTH
Manufacturer: Argento sc by sicura inc.	
Category: otc | Type: HUMAN OTC DRUG LABEL
Date: 20200910

ACTIVE INGREDIENTS: BENZALKONIUM CHLORIDE 0.2 g/100 1
INACTIVE INGREDIENTS: PHENOXYETHANOL; ALOE VERA LEAF; ETHYLHEXYLGLYCERIN; PROPYLENE GLYCOL; DIDECYLDIMONIUM CHLORIDE; GLYCERIN; ALCOHOL; WATER

77731-104 PURELOGIC 100CT ALOE ANTIBACTERIAL WIPE CANISTER

Active Ingredient(s)

BENZALKONIUM CHLORIDE 0.2% v/v. Purpose: Disinfectant

Purpose

Disinfectant, ANTIBACTERIAL WIPES

Use

- Decreases bacteria on the skin that could cause diseases.
- Recommended for repeated use.

Warnings

- For external use on hands only.
- Flammable, Keep away from flame or fire.

- Do not use in or near the eyes. In case of contact, rinse eyes thoroughly with water.

When using this product keep out of eyes, in case of contact with eyes, flush throughly with water.

- Do not ingest or inhale.
- Avoid contact with broken skin.

Stop use and ask doctor if redness & irritation develop or if condition persists for more than 72 hours.

Keep out of reach of children. If swallowed, get medical help or contact a Poison Control Center immediately.

Directions

Wipe product on hands thoroughly & allow to dry, do not wipe off.

- For children under 6, Use only with adult supervision.
- Not recommended for use with infants.

Other information

- Do not store above 105℉(40.6 ℃)
  - May discolor some fabrics
  - Harmful to plastics & wood finishes

Inactive ingredients

Water(Aqua), Phenoxyethanol, Ethylhexylglycerin, Propylene Glycol, Didecyldimoniumchloride(DDAC), Glycerin, Fragrance, Ethyl Alcohol, Aloe Barbadensis Leaf Juice.

Package Label - Principal Display Panel

100 cloth in 1 bag ndc:77731-104-01